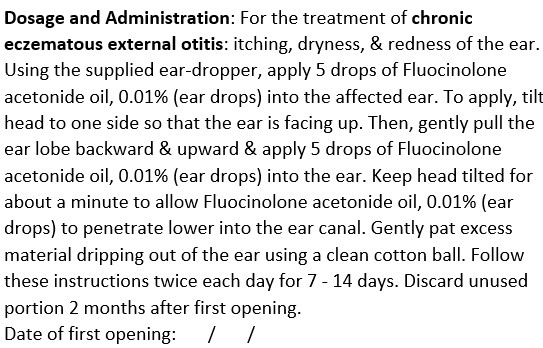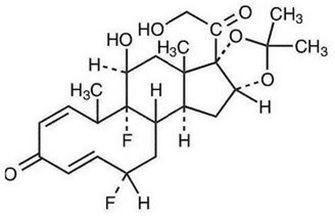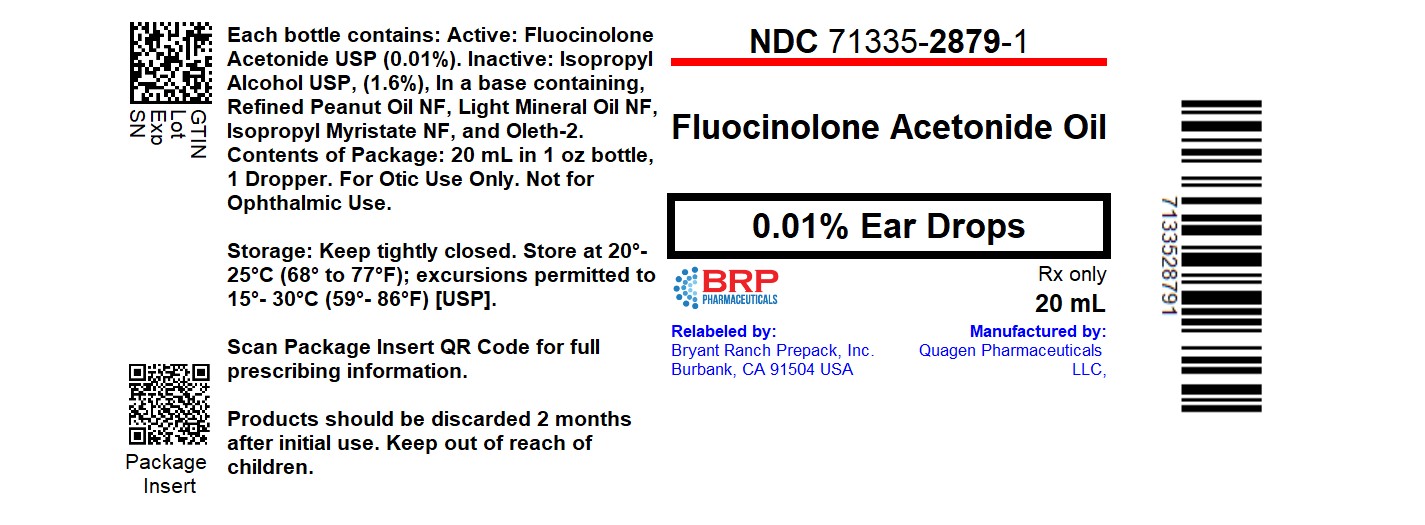 DRUG LABEL: FLUOCINOLONE ACETONIDE
NDC: 71335-2879 | Form: OIL
Manufacturer: Bryant Ranch Prepack
Category: prescription | Type: HUMAN PRESCRIPTION DRUG LABEL
Date: 20251111

ACTIVE INGREDIENTS: FLUOCINOLONE ACETONIDE 0.11 mg/1 mL

Fluocinolone Acetonide Oil, 0.01% (Ear Drops)

For Otic Use Only
Not for Ophthalmic Use

DESCRIPTION

Fluocinolone acetonide oil, 0.01% (ear drops) contain fluocinolone acetonide {(6α, 11β, 16α)-6,9- difluoro-11,21-dihydroxy-16,17[(1-methylethylidene)bis(oxy)]-pregna-1,4-diene-3,20-dione, cyclic 16,17 acetal with acetone}, a synthetic corticosteroid. This formulation is also marketed as fluocinolone acetonide topical oil, 0.01% (body oil) for the treatment of atopic dermatitis and fluocinolone acetonide topical oil, 0.01% (scalp oil) for the treatment of psoriasis of scalp. Chemically, fluocinolone acetonide is C24H30F2O6. It has the following structural formula:

Fluocinolone acetonide has a molecular weight of 452.50. It is a white crystalline powder that is odorless, stable in light, and melts at 270°C with decomposition; soluble in alcohol, acetone and methanol; slightly soluble in chloroform; insoluble in water.

Each gram of fluocinolone acetonide oil, 0.01% (ear drops) contains approximately 0.11 mg of fluocinolone acetonide in a blend of oils, which contains isopropyl alcohol, isopropyl myristate, light mineral oil, oleth-2 and refined peanut oil NF.

CLINICAL PHARMACOLOGY

Like other topical corticosteroids, fluocinolone acetonide has anti-inflammatory, antipruritic, and vasoconstrictive properties. The mechanism of the anti-inflammatory activity of the topical steroids, in general, is unclear. However, corticosteroids are thought to act by the induction of phospholipase A2 inhibitory proteins, collectively called lipocortins. It is postulated that these proteins control the biosynthesis of potent mediators of inflammation such as prostaglandins and leukotrienes by inhibiting the release of their common precursor arachidonic acid. Arachidonic acid is released from membrane phospholipids by phospholipase A2.

Pharmacokinetics: The extent of percutaneous absorption of topical corticosteroids is determined by many factors including the vehicle and the integrity of the epidermal barrier. Occlusion of topical corticosteroids can enhance penetration. Topical corticosteroids can be absorbed from normal intact skin. Also, inflammation and/or other disease processes in the skin can increase percutaneous absorption.

Fluocinolone acetonide oil, 0.01% is in the low to medium range of potency as compared with other topical corticosteroids.

CLINICAL STUDIES

Efficacy in a placebo-controlled study for the treatment of chronic eczematous external otitis on 154 patients (adults and children 2 years of age and older) treated with five drops per ear of fluocinolone acetonide oil, 0.01% twice daily, after 7 days of treatment, showed fluocinolone acetonide oil, 0.01% to be superior to placebo in clearing the signs and symptoms of eczematous external otitis.

Clinical safety studies were conducted on the same formulation of fluocinolone acetonide oil, 0.01%. Open-label safety studies on 33 children (20 subjects ages 2 to 6 years, 13 subjects ages 7 to 12 years) with moderate to severe stable atopic dermatitis, and baseline body surface area involvement greater than 75% in 18 patients, and 50% to 75% in 15 patients, were treated with fluocinolone acetonide oil, 0.01% twice daily for 4 weeks. Morning pre-stimulation cortisol level and post-Cortrosyn stimulation cortisol level were obtained in each subject at the beginning of the trial and at the end of 4 weeks of treatment. At the end of treatment, 4 out of 18 subjects aged 2 to 5 years showed low pre-stimulation cortisol levels (3.2 to 6.6 µg/dL; normal: cortisol > 7µg/dL) but all had normal responses to 0.25 mg of Cortrosyn stimulation (cortisol > 18 µg/dL).

A clinical study was conducted to assess the safety of fluocinolone acetonide oil, 0.01%, which contains refined peanut oil, on subjects with known peanut allergies. The study enrolled 13 patients with atopic dermatitis, 6 to 17 years of age. Of the 13 patients, 9 were Radioallergosorbent Test (RAST) positive to peanuts and 4 had no peanut sensitivity (controls). The study evaluated the responses to both prick test and patch test utilizing peanut oil NF, fluocinolone acetonide oil, 0.01% and histamine/saline controls on the 13 individuals. These subjects were also treated with fluocinolone acetonide oil, 0.01% twice daily for 7 days. Prick test and patch test results for all 13 patients were negative to fluocinolone acetonide oil, 0.01% and the refined peanut oil. One of the 9 peanut-sensitive patients experienced an exacerbation of atopic dermatitis after 5 days of fluocinolone acetonide oil, 0.01% use. Importantly, the bulk peanut oil used in fluocinolone acetonide oil, 0.01% is heated at 475°F for at least 15 minutes, which should provide for adequate decomposition of allergenic proteins.

INDICATION AND USAGE

Fluocinolone acetonide oil, 0.01% is a low to medium potency corticosteroid indicated for the treatment of chronic eczematous external otitis in adults and pediatric patients 2 years and older.

CONTRAINDICATIONS

Fluocinolone acetonide oil, 0.01% is contraindicated in those patients with a history of hypersensitivity to any of the components of the preparation.

This product contains refined peanut oil NF (see PRECAUTIONS).

PRECAUTIONS

General: Systemic absorption of topical corticosteroids can produce reversible hypothalamic-pituitary-adrenal (HPA) axis suppression with the potential for glucocorticosteroid insufficiency after withdrawal of treatment. Manifestations of Cushing's syndrome, hyperglycemia, and glucosuria can also be produced in some patients by systemic absorption of topical corticosteroids while on treatment.

Patients applying a topical steroid to a large surface area or to areas under occlusion should be evaluated periodically for evidence of HPA axis suppression. This may be done by using the ACTH stimulation, A.M. plasma cortisol, and urinary free cortisol tests.

If HPA axis suppression is noted, an attempt should be made to withdraw the drug, to reduce the frequency of application, or to substitute a less potent corticosteroid. Infrequently, signs and symptoms of glucocorticoid insufficiency may occur requiring supplemental systemic corticosteroids. For information on systemic supplementation, see prescribing information for those products.

Children may be more susceptible to systemic toxicity from equivalent doses due to their larger skin surface to body mass ratios. (see PRECAUTIONS-Pediatric use)

Allergic contact dermatitis to any component of topical corticosteroids is usually diagnosed by a failure to heal rather than noting a clinical exacerbation, which may occur with most topical products not containing corticosteroids. Such an observation should be corroborated with appropriate diagnostic testing. One peanut-sensitive child experienced a flare of his atopic dermatitis after 5 days of twice daily treatment with fluocinolone acetonide oil, 0.01% (see CLINICAL STUDIES section).

If wheal and flare type reactions (which may be limited to pruritus) or other manifestations of hypersensitivity develop, fluocinolone acetonide oil, 0.01% should be discontinued immediately and appropriate therapy instituted.

If concomitant skin infections are present or develop, an appropriate antifungal or antibacterial agent should be used. If a favorable response does not occur promptly, use of fluocinolone acetonide oil, 0.01% should be discontinued until the infection has been adequately controlled.

Fluocinolone acetonide oil, 0.01% is formulated with 48% refined peanut oil NF. Physicians should use caution in prescribing fluocinolone acetonide oil, 0.01% for peanut-sensitive individuals.

Information for Patients: Patients using topical corticosteroids should receive the following information and instructions:
1. This medication is to be used as directed by the physician. It is for external use only. Do not use occlusive dressings.
2. Avoid contact with the eyes. In case of contact, wash eyes liberally with water.
3. This medication should not be used for any disorder other than that for which it was prescribed.
4. Patients should promptly report to their physician any worsening of their skin condition.
5. As with other corticosteroids, therapy should be discontinued when control is achieved. If no improvement is seen within 2 weeks, contact the physician.

Laboratory Tests: The following tests may be helpful in evaluating patients for HPA axis suppression:

ACTH stimulation test
A.M. plasma cortisol test
Urinary free cortisol test

Carcinogenesis, mutagenesis, and impairment of fertility: Long-term animal studies have not been performed to evaluate the carcinogenic potential or the effect on fertility of fluocinolone acetonide oil, 0.01%. Studies have not been performed to evaluate the mutagenic potential of fluocinolone acetonide, the active ingredient in fluocinolone acetonide oil, 0.01%. Some corticosteroids have been found to be genotoxic in various genotoxicity tests (i.e. the in vitro human peripheral blood lymphocyte chromosome aberration assay with metabolic activation, the in vivo mouse bone marrow micronucleus assay, the Chinese hamster micronucleus test and the in vitro mouse lymphoma gene mutation assay).

Pregnancy: Teratogenic effects: Corticosteroids have been shown to be teratogenic in laboratory animals when administered systemically at relatively low dosage levels. Some corticosteroids have been shown to be teratogenic after dermal application in laboratory animals.

There are no adequate and well-controlled studies in pregnant women on teratogenic effects from fluocinolone acetonide oil, 0.01%. Therefore, fluocinolone acetonide oil, 0.01% should be used during pregnancy only if the potential benefit justifies the potential risk to the fetus.

Nursing Mothers: Systemically administered corticosteroids appear in human milk and could suppress growth, interfere with endogenous corticosteroid production, or cause other untoward effects. It is not known whether topical administration of corticosteroids could result in sufficient systemic absorption to produce detectable quantities in human milk. Because many drugs are excreted in human milk, caution should be exercised when fluocinolone acetonide oil, 0.01% is administered to a nursing woman.

Pediatric Use: Fluocinolone acetonide oil, 0.01% may be used twice daily for up to 2 weeks in pediatric patients 2 years of age and older with chronic eczematous external otitis.

Fluocinolone acetonide oil, 0.01% is not recommended for use on the face (see ADVERSE REACTIONS section).

Because of a higher ratio of skin surface area to body mass, children are at a greater risk than adults of HPA-axis-suppression when they are treated with topical corticosteroids. They are therefore also at greater risk of glucocorticosteroid insufficiency after withdrawal of treatment and of Cushing's syndrome while on treatment. Adverse effects including striae have been reported with inappropriate use of topical corticosteroids in infants and children. (see PRECAUTIONS).

HPA axis suppression, Cushing's syndrome, and intracranial hypertension have been reported in children receiving topical corticosteroids. Children may be more susceptible to systemic toxicity from equivalent doses due to their larger skin surface to body mass ratios. Manifestations of adrenal suppression in children include linear growth retardation, delayed weight gain, low plasma cortisol levels, and absence of response to ACTH stimulation. Manifestations of intracranial hypertension include bulging fontanelles, headaches, and bilateral papilledema.

Fluocinolone acetonide oil, 0.01% is formulated with 48% refined peanut oil NF. Physicians should use caution in prescribing fluocinolone acetonide oil, 0.01% for peanut-sensitive individuals.

ADVERSE REACTIONS

The following local adverse reactions have been reported infrequently with topical corticosteroids. They may occur more frequently with the use of occlusive dressings, especially with higher potency corticosteroids. These reactions are listed in an approximate decreasing order of occurrence: burning, itching, irritation, dryness, folliculitis, acneiform eruptions, hypopigmentation, perioral dermatitis, allergic contact dermatitis, secondary infection, skin atrophy, striae, and miliaria. One peanut sensitive child experienced a flare of his atopic dermatitis after 5 days of twice daily treatment with fluocinolone acetonide oil, 0.01%.

To report SUSPECTED ADVERSE REACTIONS, contact Quagen Pharmaceuticals LLC at 1-888-344-9603 or FDA at 1-800-FDA-1088 or www.fda.gov/medwatch.

OVERDOSAGE

Topically applied fluocinolone acetonide oil, 0.01% can be absorbed in sufficient amounts to produce systemic effects (see PRECAUTIONS).

DOSAGE AND ADMINISTRATION

For the treatment of chronic eczematous external otitis, using the supplied ear-dropper, apply 5 drops of fluocinolone acetonide oil, 0.01% into the affected ear. To apply, tilt head to one side so that the ear is facing up. Then, gently pull the ear lobe backward and upward and apply 5 drops of fluocinolone acetonide oil, 0.01% into the ear. Keep head tilted for about a minute to allow fluocinolone acetonide oil, 0.01% to penetrate lower into the ear canal. Gently pat excess material dripping out of the ear using a clean cotton ball. Follow these instructions twice each day for 7 to 14 days.

HOW SUPPLIED

Fluocinolone acetonide oil, 0.01% (ear drops) is supplied in a 1 fluid ounce bottle containing 20 mL net content (Dropper Included). (NDC # 71335-2879-1).

Keep tightly closed. Store at 20°-25° C (68° to 77° F); excursions permitted to 15°-30° C (59°-86°F.) [see USP Controlled Room Temperature].

Discard fluocinolone acetonide oil, 0.01% (ear drops) 2 months after initial use.

Repackaged/Relabeled by:
Bryant Ranch Prepack, Inc.
Burbank, CA 91504

PACKAGE LABEL

Fluocinolone Acetonide 0.01% Oil #20 OTIC